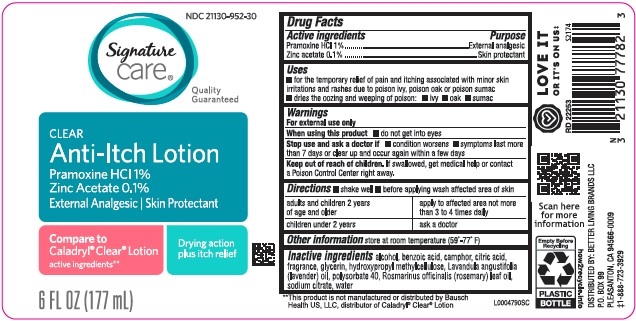 DRUG LABEL: Clear Anti Itch
NDC: 21130-952 | Form: LOTION
Manufacturer: Better Living Brands, LLC
Category: otc | Type: HUMAN OTC DRUG LABEL
Date: 20260223

ACTIVE INGREDIENTS: PRAMOXINE HYDROCHLORIDE 10 mg/1 mL; ZINC ACETATE 1 mg/1 mL
INACTIVE INGREDIENTS: ALCOHOL; BENZOIC ACID; CAMPHOR (NATURAL); CITRIC ACID MONOHYDRATE; GLYCERIN; HYPROMELLOSE, UNSPECIFIED; LAVENDER OIL; POLYSORBATE 40; ROSEMARY OIL; SODIUM CITRATE; WATER

Signature Care 218.002/218AF
Clear Anti-Itch Lotion

Active Ingredients

Pramoxine HCl 1%

Zinc acetate 0.1%

Purpose

External analgesic

Skin protectant

Uses

- for the temporary relief of pain and itching associated with minor skin irritations and rashes due to poison ivy, poison oak or poison sumac
- dries the oozing and weeping of poison:
- ivy
- oak
- sumac

Warnings

For external use only

when using this product

do not get into eyes

Stop use and ask a doctor if

- condition worsens
- symptoms last more than 7 days or clear up and occur again within a few days

Keep out of reach of children.

If swallowed, get medical help or contact a Poison Control Center right away.

Directions

- shake well
- before applying wash affected area of skin

adults and children 2 years of age and older - apply to affected area not more than 3 to 4 times daily

children under 2 years of age - ask a doctor

other information

store at room temperature (59°-77°F)

Inactive ingredients

alcohol, benzoic acid, camphor, citric acid, fragrance, glycerin, hydroxypropyl methylcellulose, Lavandula angustifolia (lavender) oil, polysorbate 40, Rosmarinus officinalis (rosemary) leaf oil, sodium citrate, water

Disclaimer

**This product is not manufactured or distributed by Bausch Health US, LLC, distributor of Caladryl®Clear®Lotion.

ADVERSE REACTION

Scan here for more information

Empty Before Recycling

PLASTIC BOTTLE

how2recycle.info

DISTRIBUTED BY: BETTER LIVING BRANDS LLC

P.O. BOX 99

PLEASANTON, CA 94566-0009

‡1-888-723-3929

LOVE IT OR IT'S ON US

principal display panel

NDC 21130-952-30

Signature Care®

Quality Guaranteed

CLEAR

Anti-Itch Lotion

Pramoxine HCl 1%

Zinc Acetate 0.1%

External Analgesic/Skin Protectant

Compare to Caladryl®Clear®Lotion active ingredients**

Drying action plus itch relief

6 FL OZ (177 mL)